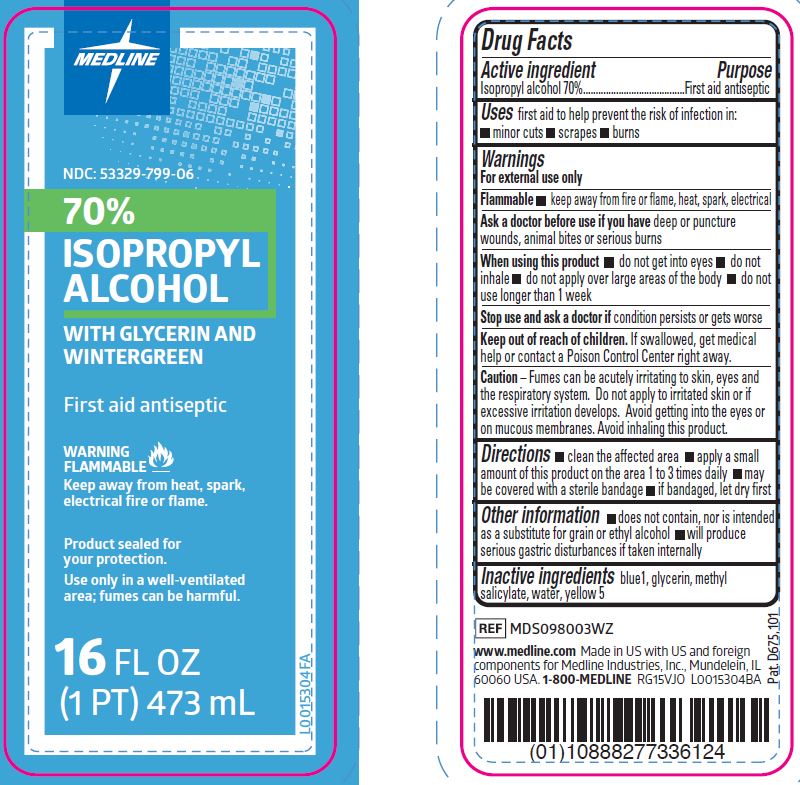 DRUG LABEL: Isopropyl alcohol
NDC: 53329-799 | Form: SOLUTION
Manufacturer: Medline Industries, LP
Category: otc | Type: HUMAN OTC DRUG LABEL
Date: 20260211

ACTIVE INGREDIENTS: ISOPROPYL ALCOHOL 70 mL/100 mL
INACTIVE INGREDIENTS: FD&C YELLOW NO. 5; FD&C BLUE NO. 1; GLYCERIN; METHYL SALICYLATE; WATER

799 Isopropyl Alcohol (wintergreen)

Active ingredient

Isopropyl alcohol 70%

Purpose

First aid antiseptic

Uses

first aid to help prevent the risk of infection in:

- minor cuts
- scrapes
- burns

Warnings

For external use only

Flammable. Keep away from fire or flame, heat, spark, electrical.

Ask a doctor before use if you have

deep or puncture wounds, animal bites or serious burns

When using this product

- do not get into eyes
- do not inhale
- do not apply over large areas of the body
- do not use longer than 1 week

Stop use and ask a doctor if

condition persists or gets worse

Keep out of reach of children.

If swallowed, get medical help or contact a Poison Control Center right away.

Caution

Fumes can be acutely irritating to skin, eyes and the respiratory system. Do not apply to irritated skin or if excessive irritation develops. Avoid getting into the eyes or on mucous membranes. Avoid inhaling this product.

Directions

- clean the affected area
- apply a small amount of this product on the area 1 to 3 times daily
- may be covered with a sterile bandage
- if bandaged, let dry first

Other information

- does not contain, nor is intended as a substitute for grain or ethyl alcohol
- will produce serious gastric disturbances if taken internally

Inactive ingredients

blue 1, glycerin, methyl salicylate, water, yellow 5

Manufacturing Information

www.medline.com

Made in US with US and foreign components

for Medline Industries, Inc.

Mundelein, IL 60060 USA

1-800-MEDLINE

REF: MDS098003WZ